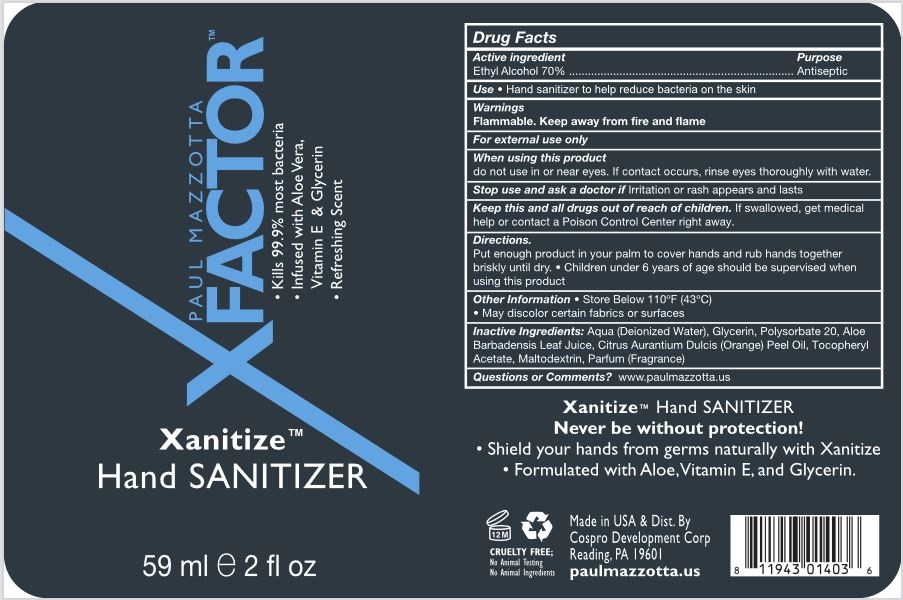 DRUG LABEL: Xanitize
NDC: 46607-114 | Form: SOLUTION
Manufacturer: Cospro Development Corp
Category: otc | Type: HUMAN OTC DRUG LABEL
Date: 20210505

ACTIVE INGREDIENTS: ALCOHOL 70 mL/100 mL
INACTIVE INGREDIENTS: ORANGE PEEL; MALTODEXTRIN; GLYCERIN; WATER; ISOPROPYL MYRISTATE; ALOE VERA LEAF; ALLYL METHACRYLATE/GLYCOL DIMETHACRYLATE CROSSPOLYMER; AMINOMETHYLPROPANOL

This is a hand sanitizer manufactured according to the Temporary Policy for Preparation of Certain Alcohol-Based Hand Sanitizer Products During the Public Health Emergency (CoViD-19); Guidance for Industry.

The hand sanitizer is manufactured using only the following United States Pharmacopoeia (USP) grade ingredients in the preparation of the product (percentage in final product formulation) consistent with World Health Organization (WHO) recommendations:

1. Alcohol (ethanol)
2. Glycerol.
3. Sterile distilled water.

Active Ingredient(s)

Alcohol 70%. Purpose: Antiseptic

Purpose

Antiseptic, Hand Sanitizer

Use

Hand Sanitizer to help reduce bacteria on the skin.

Warnings

For external use only. Flammable. Keep away from fire and flame

- do not use in or near eyes

When using this product do not use in or near eyes. If contact occurs, rinse eyes thoroughly with water.
Stop use and ask a doctor if irritation or rash appears and lasts.
Keep out of reach of children. If swallowed, get medical help or contact a Poison Control Center right away.

Stop use and ask a doctor if irritation or rash appears and lasts.

Keep out of reach of children. If swallowed, get medical help or contact a Poison Control Center right away.

Directions

- Place enough product in your palm to cover hand and rub together briskly until dry.
- Supervise children under 6 years of age when using this product to avoid swallowing.

Other information

- Store below 110° F (43º)

Inactive ingredients

glycerin, tocopheryl acetate, purified water, aloe barbadensis leaf juice, maltodextrin, citrus aurantium dulcis peel oil, acrylates/C10-30 Alkyl Acrylate Crosspolymer, Aminomethyl Propanol